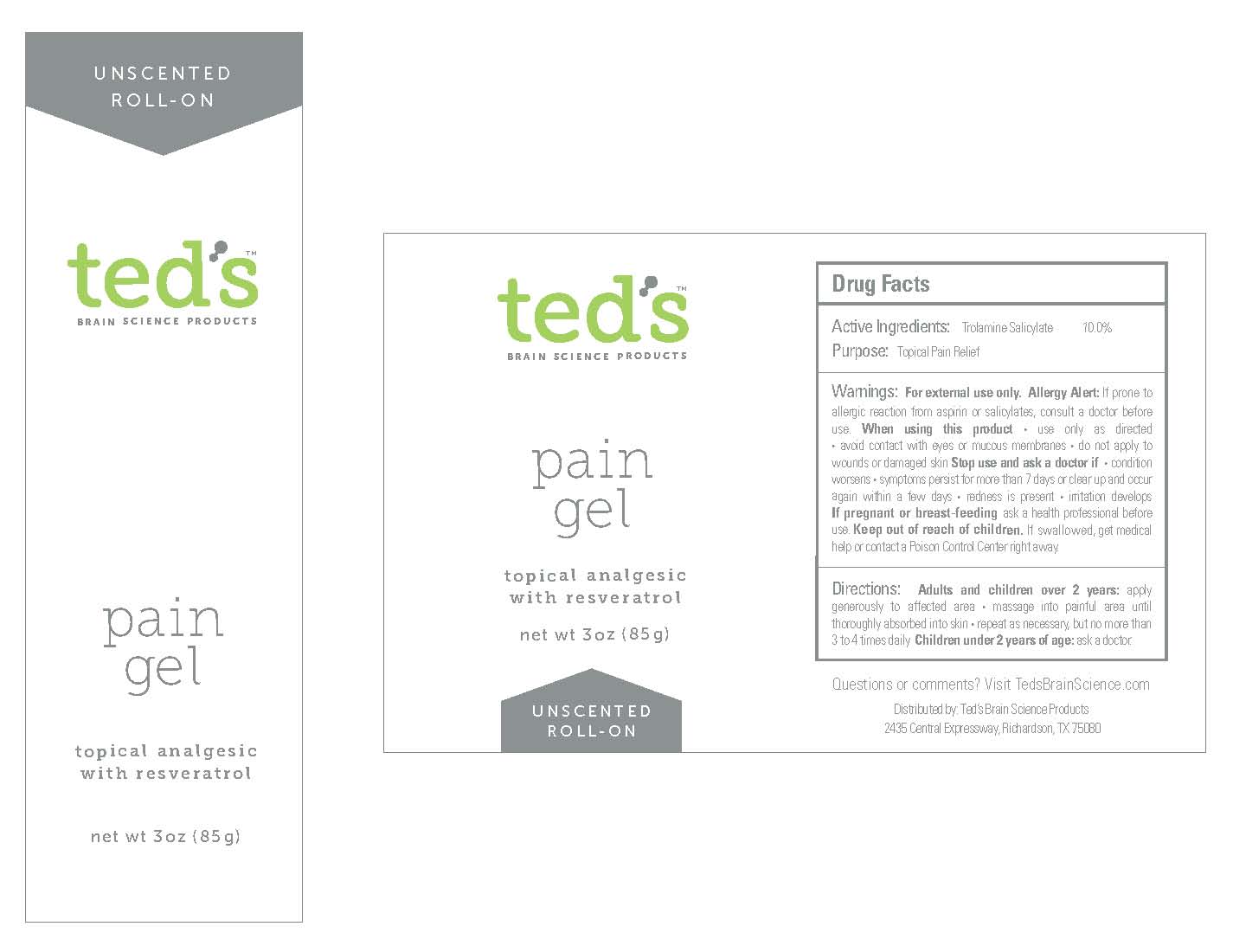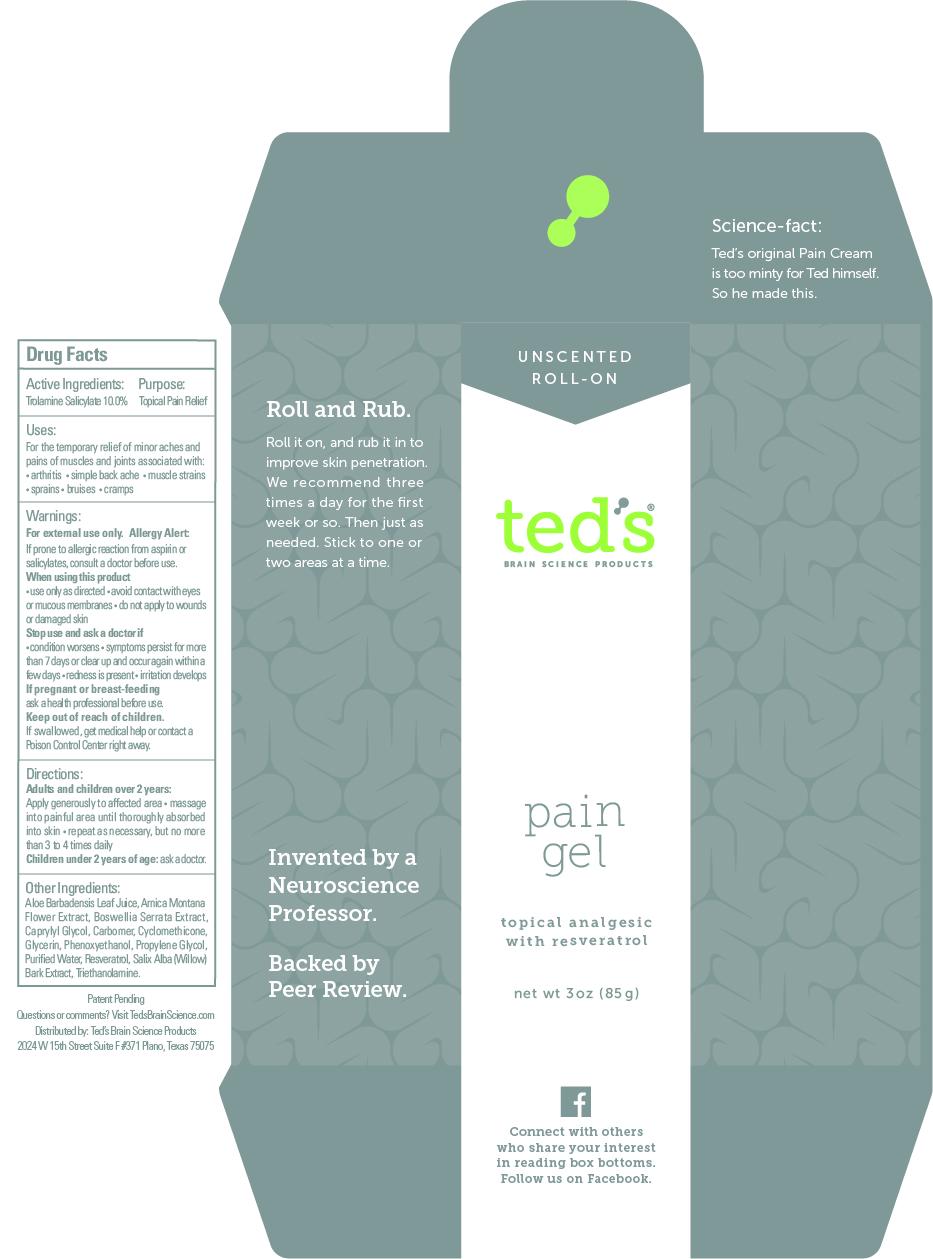 DRUG LABEL: teds topical pain gel roll on
NDC: 58133-211 | Form: GEL
Manufacturer: Cosmetic Specialty Labs, Inc.
Category: otc | Type: HUMAN OTC DRUG LABEL
Date: 20210111

ACTIVE INGREDIENTS: TROLAMINE SALICYLATE 10 g/100 g
INACTIVE INGREDIENTS: ALOE VERA LEAF; CARBOMER 940; CYCLOMETHICONE; TRIETHANOLAMINE ISOSTEARATE; CAPRYLYL GLYCOL; PROPYLENE GLYCOL DIETHYLHEXANOATE; SALIX ALBA BARK; BOSWELLIA SERRATA RESIN OIL; ARNICA MONTANA FLOWER; WATER; RESVERATROL; GLYCERIN; PHENOXYETHANOL

ted's Brain Science Products pain gel

Active ingredient

Trolamine Salicylate - 10%

Purpose

Topical Pain Relief

Uses

For the temporarily relief of minor aches and pains of muscles and joints associated with: • arthritis • simple back ache • muscle strains • sprains • bruises • cramps

Warnings

For external use only

Allergy Alert

If prone to allergic reaction from aspirin or salicylates, consult a doctor before use.

When using this product

• use only as directed • avoid contact with eyes or mucous membranes • do not apply to wounds or damaged skin

Stop use and ask a doctor if

• condition worsens • symptoms persist for more than 7 days or clear up and occur again within a few days • redness is present

• irritation develops

If pregnant or breast-feeding

ask a health professional before use.

Keep out of reach of children

If swallowed, get medical help or contact a Poison Control Center right away.

Directions

Use only as directed

Adults and children over 2 years:

- Apply generously to affected area
- massage into painful area until thoroughly absorbed
- into skin
- repeat as necessary, but no more than 3 to 4 times daily

children under 2 years of age: Ask a doctor

Inactive ingredients:

Aloe Barbadensis Leaf Juice, Arnica Montana Flower Extract, Boswellia Serrata Extract, Caprylyl Glycol, Carbomer, Cyclomethicone, Glycerin, Phenoxyethanol, Propylene Glycol, Purified Water, Resveratrol, Salix Alba (Willow) Bark Extract, Triethanolamine.